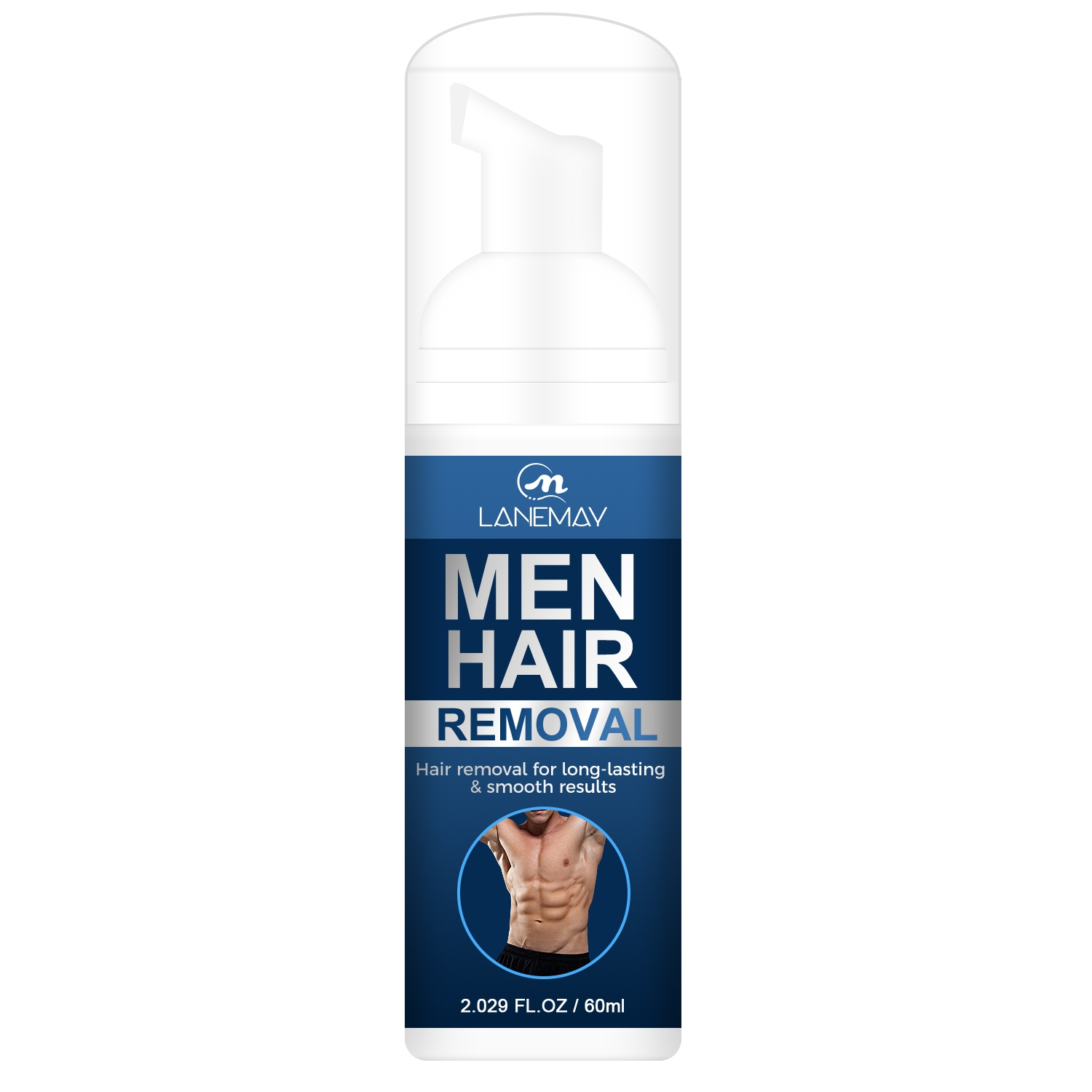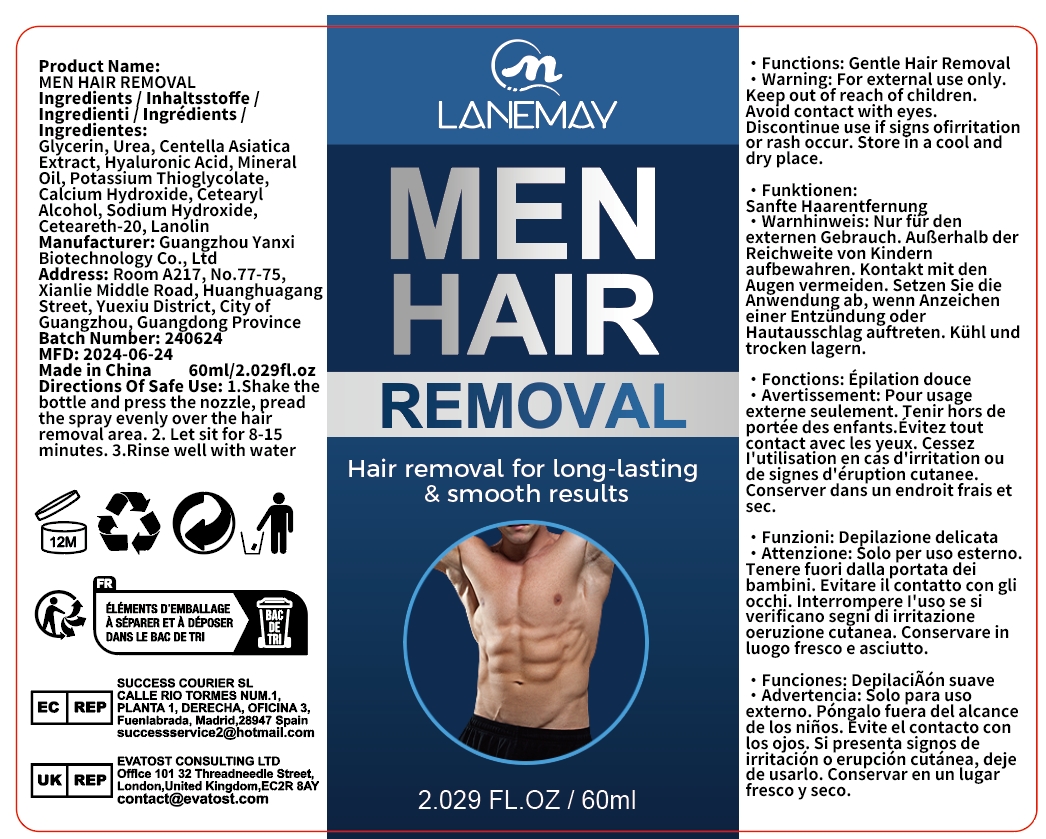 DRUG LABEL: MEN HAIR REMOVAL
NDC: 84025-183 | Form: CREAM
Manufacturer: Guangzhou Yanxi Biotechnology Co.. Ltd
Category: otc | Type: HUMAN OTC DRUG LABEL
Date: 20240907

ACTIVE INGREDIENTS: GLYCERIN 5 mg/60 mL; HYALURONIC ACID 3 mg/60 mL
INACTIVE INGREDIENTS: WATER

DOSAGE AND ADMINISTRATION

For men's body hair removal

WARNINGS

keep out of children

INACTIVE INGREDIENT

AQUA

INDICATIONS AND USAGE

For daily men's skin care

keep out of children

PURPOSE

Gently removes men's body hair and keeps the skin dry